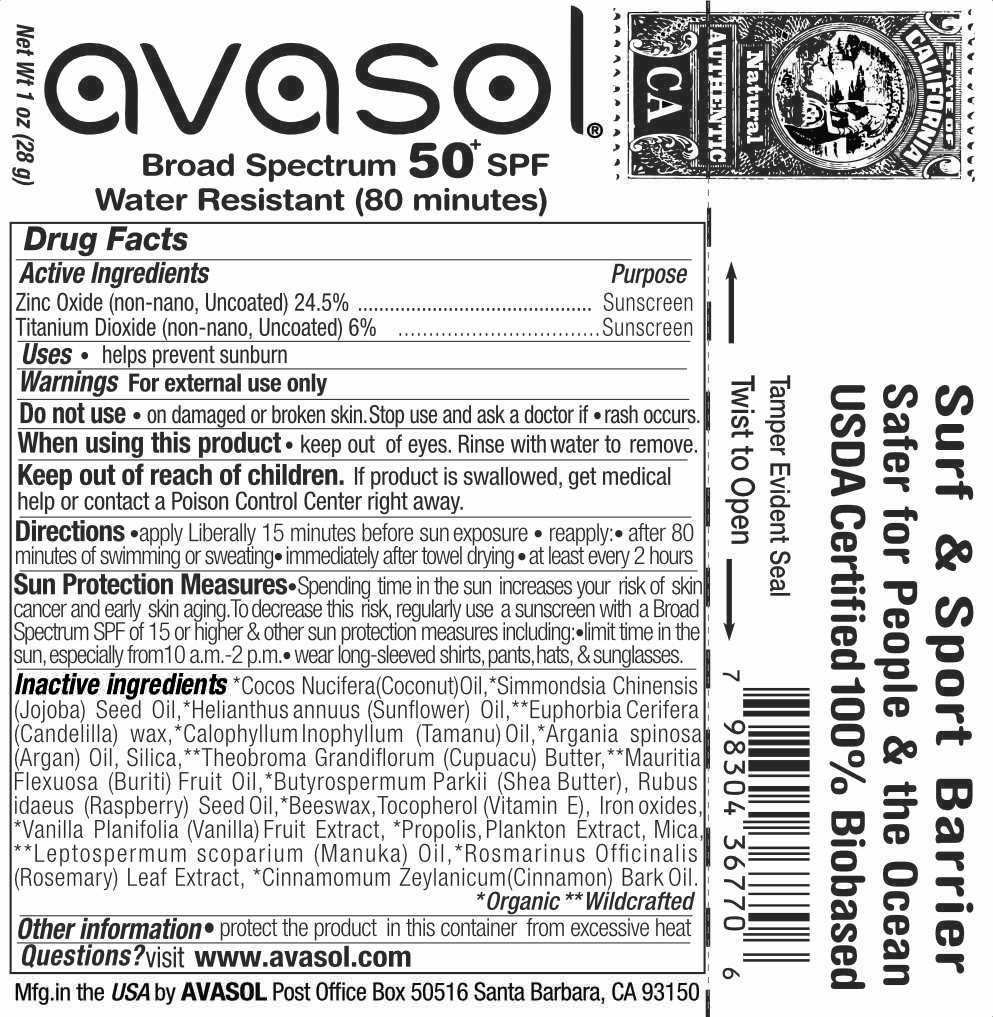 DRUG LABEL: SURFERS BARRIER SPF 50
NDC: 58518-021 | Form: STICK
Manufacturer: Avasol LLC
Category: otc | Type: HUMAN OTC DRUG LABEL
Date: 20260126

ACTIVE INGREDIENTS: ZINC OXIDE 24.5 g/100 g; TITANIUM DIOXIDE 6 g/100 g
INACTIVE INGREDIENTS: COCONUT OIL; JOJOBA OIL; SUNFLOWER OIL; CANDELILLA WAX; TAMANU OIL; ARGAN OIL; SILICON DIOXIDE; THEOBROMA GRANDIFLORUM SEED; SHEANUT; MAURITIA FLEXUOSA WHOLE; RUBUS IDAEUS SEED; YELLOW WAX; PROPOLIS WAX; TOCOPHEROL; MICA; VANILLA BEAN; HAEMATOCOCCUS PLUVIALIS; MANUKA OIL; ROSEMARY; CINNAMON BARK OIL; FERROUS OXIDE

SURFERS BARRIER SPF 50

Active Ingredients

Zinc Oxide (non-nano, Uncoated) 24.5%

Titanium Dioxide (non-nano, Uncoated) 6%

Purpose

Sunscreen

Sunscreen

Uses

- helps prevent sunburn

Warnings

- For external use only.
- Keep out of eyes. Rinse with water to remove.

Stop use and ask a doctor if rash or irritation occurs.

Do not use if allergic to ingredients, or nuts. Test small area first.

Keep out of reach of children. If swallowed, get medical help right away.

Directions

- apply liberally before sun
- reapply: after 80 min. of swimming or sweating, immediately after towel drying, or as needed
- children under 6 months: Ask a doctor.

Inactive ingredients

*Cocos Nucifera (Coconut) Oil, *Simmondsia Chinensis (Jojoba) Seed Oil, *Helianthus annuus (Sunflower) Oil, **Euphorbia Cerifera (Candelilla) wax *Calophyllum Inophyllum (Tamanu) Oil, *Argania spinosa (Argan) Oil, Silica, **Theobroma Grandiflorum (Cupuacu) Butter, **Mauritia Flexuosa (Buriti) Fruit Oil, *Butyrospermum Parkii (Shea Butter), Rubus idaeus (Raspberry) Seed Oil, *Beeswax, Tocopherol(Vitamin E), Iron oxides, Vanilla Planifolia (Vanilla) Fruit Extract, *Propolis, Plankton Extract, Mica, **Leptospermum scoparium (Manuka) Oil, *Rosmarinus Officinalis (Rosemary) Leaf Extract, *Cinnamomum Zeylanicum(Cinnamon) Bark Oil. **Organic **Wildcrafted

Other information

- protect package from moisture & extreme heat.

Questions?

visit www.avasol.com

Principal Display Panel – Tube Label

avasol®

mineral sunscreen

50+ SPF

Net Wt 1 oz (28 g)